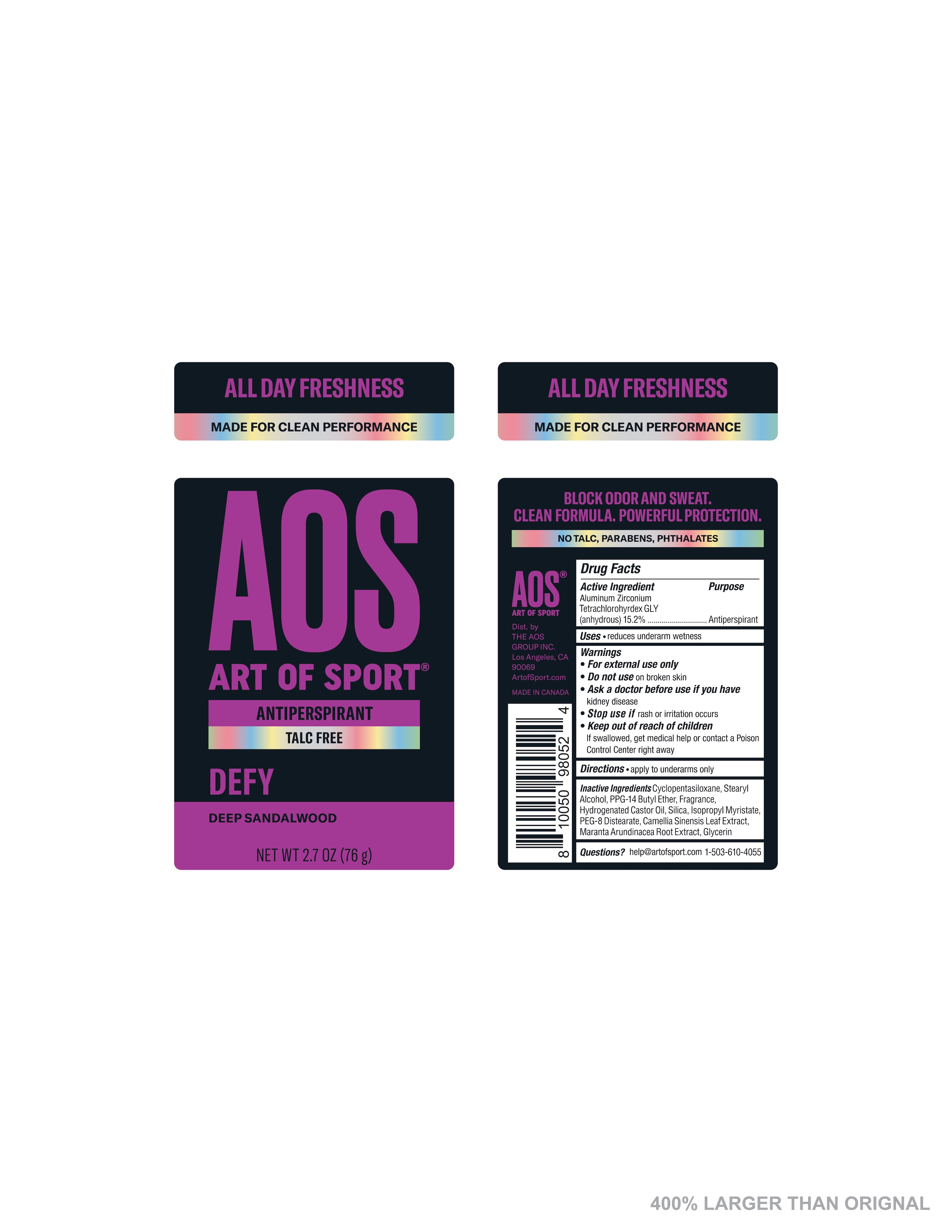 DRUG LABEL: ART OF SPORT ANTIPERSPIRANT DEFY
NDC: 72698-605 | Form: STICK
Manufacturer: AOS GROUP INC, THE
Category: otc | Type: HUMAN OTC DRUG LABEL
Date: 20230130

ACTIVE INGREDIENTS: ALUMINUM ZIRCONIUM TETRACHLOROHYDREX GLY 15.2 g/100 g
INACTIVE INGREDIENTS: STEARYL ALCOHOL; CYCLOMETHICONE 5; ISOPROPYL MYRISTATE; PPG-14 BUTYL ETHER; SILICON DIOXIDE; PEG-8 DISTEARATE; GREEN TEA LEAF; MARANTA ARUNDINACEA ROOT; GLYCERIN; HYDROGENATED CASTOR OIL

Antiperspirant. Defy flavor

Active Ingredient

Aluminum Zirconium Tetrachlorohydrex Gly (15.2%)

Purpose
Antiperspirant

Uses
reduces underarm wetness

Warnings
* For external use only
* Do not use on broken skin
* Ask a doctor before use if you have
kidney disease
* Stop use if rash or irritation occurs

* Keep out of reach of children
If swallowed, get medical help or contact a Poison Control Center right away

Directions
apply to underarms only

Inactive Ingredients
Cyclopentasiloxane, Stearyl Alcohol, PPG-14 Butyl Ether, Fragrance, Hydrogenated Castor Oil, Silica, Isorpropyl Myristate, PEG-8 Distearate, Camellia Sinensis Leaf Extract, Maranta Arundinacea Root Extract, Glycerin

Questions?
help@artofsport.com 1-503-610-4055